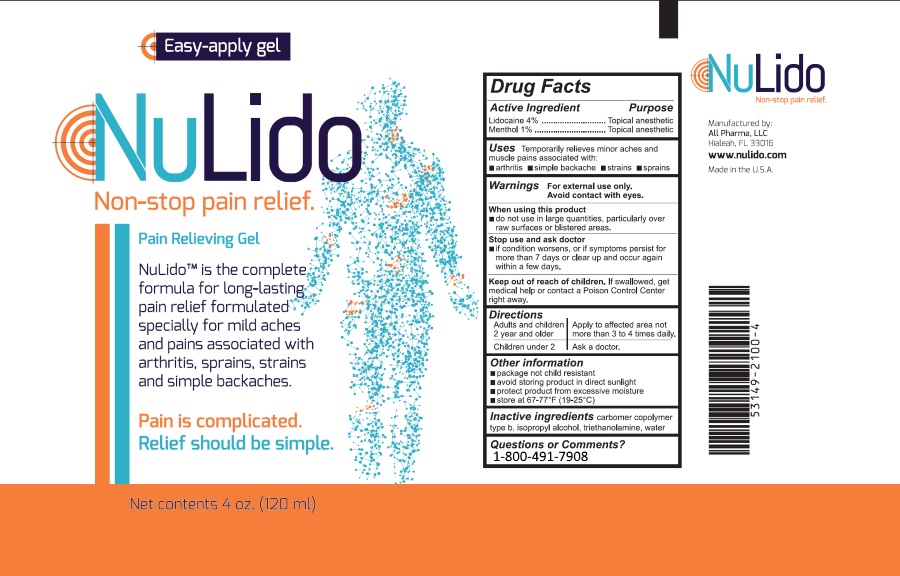 DRUG LABEL: NuLido
NDC: 53149-2100 | Form: GEL
Manufacturer: All Pharma LLC
Category: otc | Type: HUMAN OTC DRUG LABEL
Date: 20171018

ACTIVE INGREDIENTS: LIDOCAINE 4 mg/1 mL; MENTHOL 1 mg/1 mL
INACTIVE INGREDIENTS: CARBOMER COPOLYMER TYPE B (ALLYL PENTAERYTHRITOL CROSSLINKED) ; ISOPROPYL ALCOHOL; TROLAMINE; WATER

NuLido

Active Ingedients

Each milliliter contains
Active Ingredient | Purpose
Lidocaine Hydrochloride 4.0% | Topical Anesthetic
Menthol 1.0% | Topical Anesthetic

INACTIVE INGREDIENT

Carbomer copolymer type b, Isopropyl Alcohol, water, trolamine

Warnings

For external use only.

Keep out of reach of children

If swallowed, get medical help or contact a Poison Control Center right away. Package not child resistant.

When using this product

■ avoid contact with eyes, genitals, and other mucous membranes. If eye contact occurs, rinse thoroughly with water.
■ do not use on open wounds, cuts, damaged or infected skin
■ do not use With a bandage or a heating pad

Ask your doctor before use if

■ you are allergic to any ingredients
■ you are pregnant or breast-feeding

Uses

Temporarily relieves minor aches and muscle pains associated with:

■ arthritis

■ simple back pain

■ strains

■ muscle soreness

Purpose

Temporarily relieves minor aches and muscle pains associated with:

■ arthritis
■ simple back pain
■ strains
■ muscle soreness

Dosage & Administration

Apply to the affected area.
Adults and children 12 years and older | Apply to the affected area. Product may be used as necessary, but should not be used more than four times per day.; Wash hands immediately afterwards.
Children under 2 | Ask a doctor

Other Information

■ avoid storing product in direct sunlight
■ protect product from excessive moisture
■ store at 67-77°F (19-25°C)

Stop Use and Ask Doctor

■ if condition worsens or symptoms persist for more than 7 days
■ if excessive skin irritation occurs

Label Image

Manufactured by:
All Pharma, LLC
Hialeah, FL 33016
www.allpharmallc.com
Made in the U.S.A.